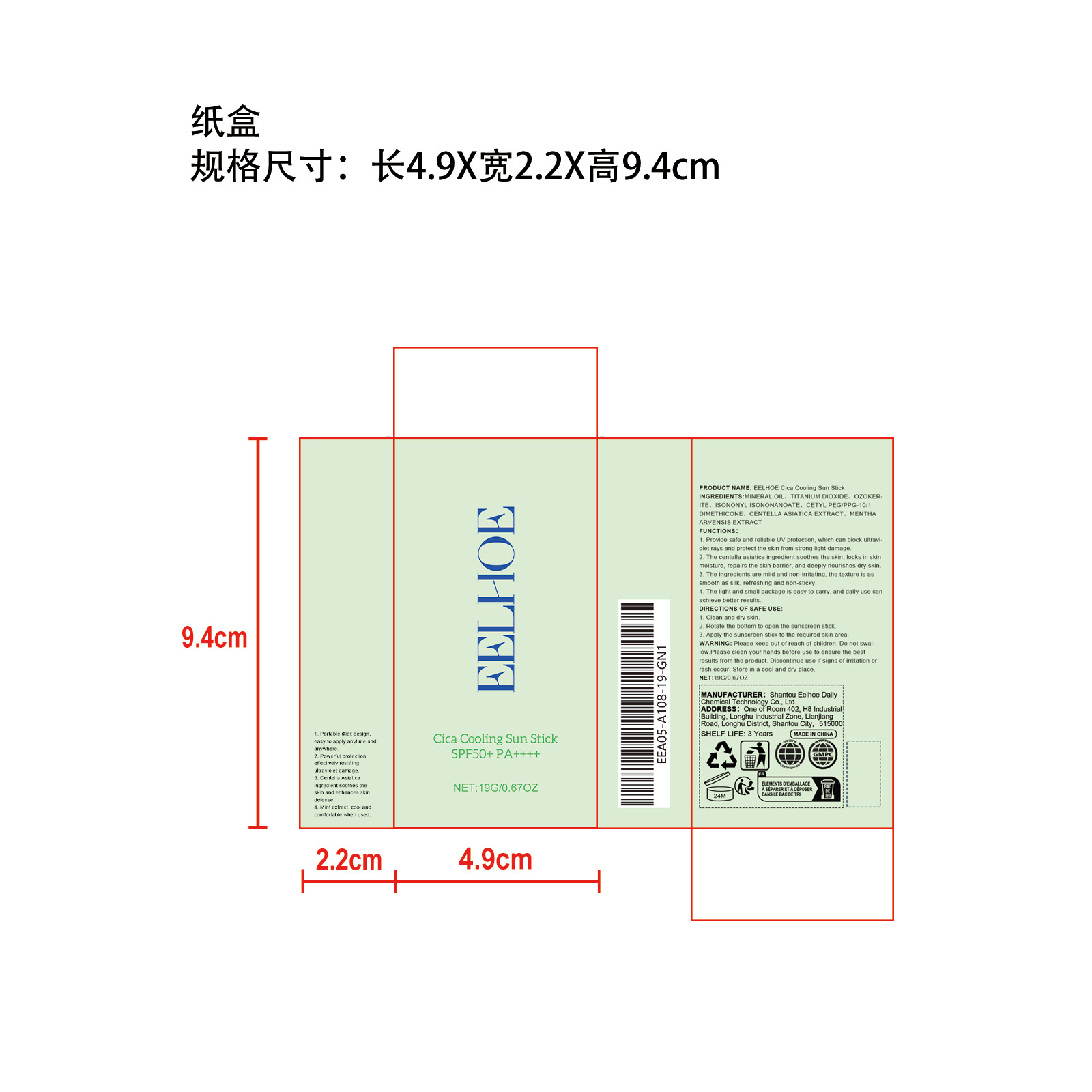 DRUG LABEL: EELHOE Cica Cooling Sun Stick
NDC: 85064-003 | Form: STICK
Manufacturer: Shantou Eelhoe Daily Chemical Technology Co., Ltd.
Category: otc | Type: HUMAN OTC DRUG LABEL
Date: 20251127

ACTIVE INGREDIENTS: MENTHA ARVENSIS LEAF 0.019 mg/19 mg; CENTELLA ASIATICA TRITERPENOIDS 0.019 mg/19 mg
INACTIVE INGREDIENTS: CERESIN 3.8 mg/19 mg; ISONONYL ISONONANOATE 1.9 mg/19 mg; HYALURONIC ACID 0.19 mg/19 mg; CETYL PEG/PPG-10/1 DIMETHICONE (HLB 4) 0.665 mg/19 mg; MINERAL OIL 7.657 mg/19 mg; TITANIUM DIOXIDE 4.75 mg/19 mg

ACTIVE INGREDIENT

MENTHA ARVENSIS LEAF、CENTELLA ASIATICA TRITERPENOIDS

PURPOSE

1. Provide safe and reliable UV protection, which can block ultraviolet rays and protect the skin from strong light damage.

2. The centella asiatica ingredient soothes the skin, locks in skin moisture, repairs the skin barrier, and deeply nourishes dry skin.

3. The ingredients are mild and non-irritating, the texture is as smooth as silk, refreshing and non-sticky.

4. The light and small package is easy to carry, and daily use can achieve better results.

WHEN USING

1. Clean and dry skin.

2. Rotate the bottom to open the sunscreen stick.

3. Apply the sunscreen stick to the required skin area.

WARNINGS

Please keep out of reach of children. Do not swallow.Please clean your hands before use to ensure the best results from the product. Discontinue use if signs of irritation or rash occur. Store in a cool and dry place.

KEEP OUT OF REACH OF CHILDREN

Please keep out of reach of children. Do not swallow.

DO NOT USE

Discontinue use if signs of irritation or rash occur.

STOP USE

Discontinue use if signs of irritation or rash occur.

STORAGE AND HANDLING

Store in a cool and dry place.

INACTIVE INGREDIENT

MINERAL OIL
TITANIUM DIOXIDE
OZOKERITE
ISONONYL ISONONANOATE
CETYL PEG/PPG-10/1 DIMETHICONE
TITANIUM DIOXIDE